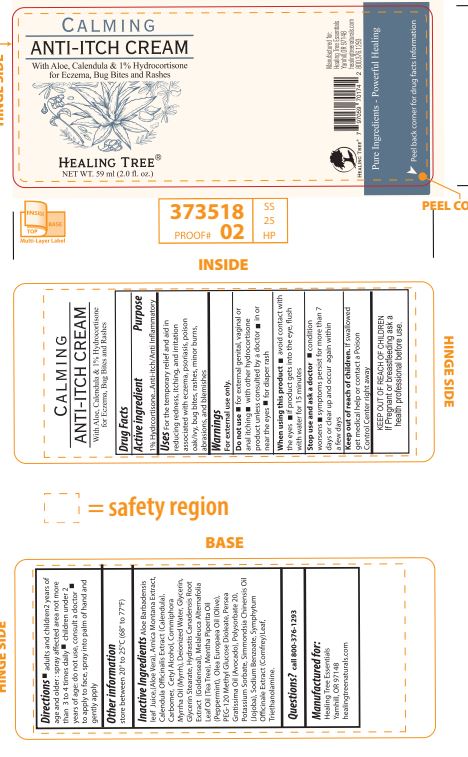 DRUG LABEL: HEALING TREE CALMING ANTI-ITCH
NDC: 76348-804 | Form: CREAM
Manufacturer: Renu Laboratories, LLC
Category: otc | Type: HUMAN OTC DRUG LABEL
Date: 20251106

ACTIVE INGREDIENTS: HYDROCORTISONE 0.59 mg/59 mL
INACTIVE INGREDIENTS: GOLDENSEAL; COMFREY; TROLAMINE; POTASSIUM SORBATE; ARNICA MONTANA FLOWER; MYRRH OIL; CETYL ALCOHOL; GLYCERYL MONOSTEARATE; MELALEUCA ALTERNIFOLIA (TEA TREE) LEAF OIL; PEPPERMINT OIL; JOJOBA OIL; PEG-120 METHYL GLUCOSE DIOLEATE; WATER; SODIUM BENZOATE; AVOCADO OIL; OLIVE OIL; CARBOMER HOMOPOLYMER, UNSPECIFIED TYPE; GLYCERIN; CALENDULA OFFICINALIS FLOWER; ALOE VERA LEAF; POLYSORBATE 20

HEALING TREE CALMING ANTI-ITCH CREAM

ACTIVE INGREDIENT

1 Percent Hydrocortisone

PURPOSE

Anti-itch Anti-inflammatory

Uses

For the temporary relief and aid in reducing redness, itching and irritation associated with eczema, psoriasis, poison oak and ivy, bug bites, rashes, minor burns, abrasions and blemishes

WARNINGS

For external use only

Do not use

- for external genital, vaginal or anal itching
- with other hydrocortisone product unless consulted by a doctor
- in or near the eyes
- for diaper rash

Stop use and ask a doctor if

- condition worsens
- symptoms persist for more than 7 days or clear up and occur again within a few days

Stop use and ask a doctor if

condition worsens
symptoms persist for more than 7 days or clear up and occur again within a few days

PREGNANCY OR BREAST FEEDING

If pregnant or breastfeeding ask a health professional before use

KEEP OUT OF REACH OF CHILDREN

If swallowed get medical help or contact a Poison Control Center right away

STATEMENT OF IDENTITY

HEALING TREE

CALMING

ANTI-ITCH CREAM

NET WT. 59 ml (2.0 fl. oz.)

Directions

- adults and children 2 years of age and older: spray affected area not more than 3 to 4 times daily
- children under 2 years of age: do not use consult a doctor
- to apply to face, spray into palm of hand and gently apply

Other information

store between 20° to 25° C (68° to 77° F)

INACTIVE INGREDIENT

Aloe Barbadensis leaf juice (Aloe Vera), Arnica Montana Extract, Calendula Officinalis Extract (Calendula), Carbomer, Cetyl Alcohol,

Commiphora Myrrha Oil (Myrrh), Deionized Water, Glycerin, Glycerol Stearate,Hydrastis Canadensis Root Extract (Goldenseal),

Melaleuca Alternifolia Leaf Oil (Tea Tree), Mentha Piperita Oil (Peppermint), Olea Europaea Oil (Olive), PEG-120 Methyl Glucose

Dioleate, Persea Gratissima Oil (Avocado), Polysorbate 20, Potassium Sorbate, Simmondsia Chinensis Oil (Jojoba), Sodium

Benzoate, Symphytum Officinale Extract (Comfrey) Leaf, Triethanolamine.

Questions? call 800-376-1293

Manufactured for

Healing Tree Essentials

Yamhill, OR 97148

healingtreenaturals.com

Multi-layer Label

Healing Tree Anti-Itch Cream